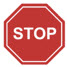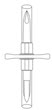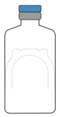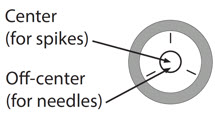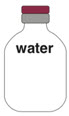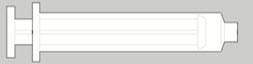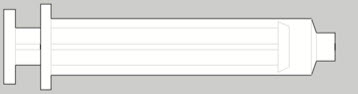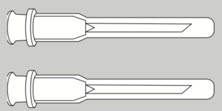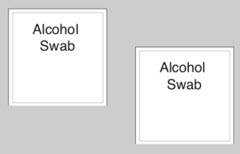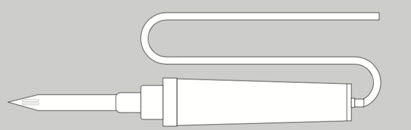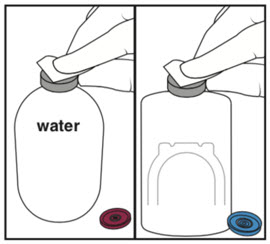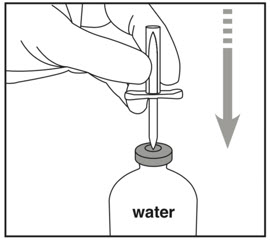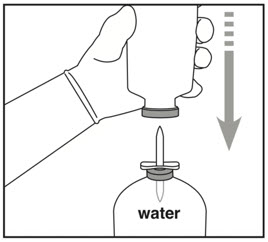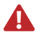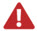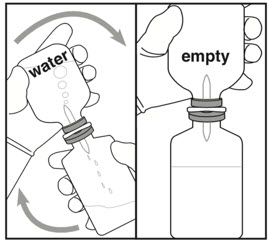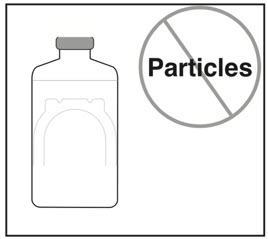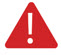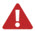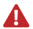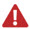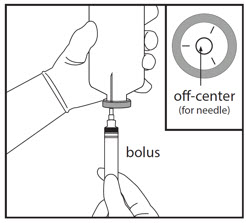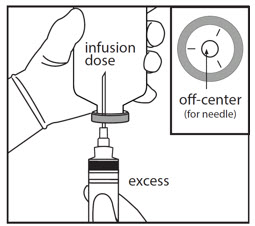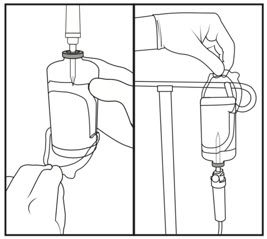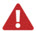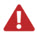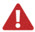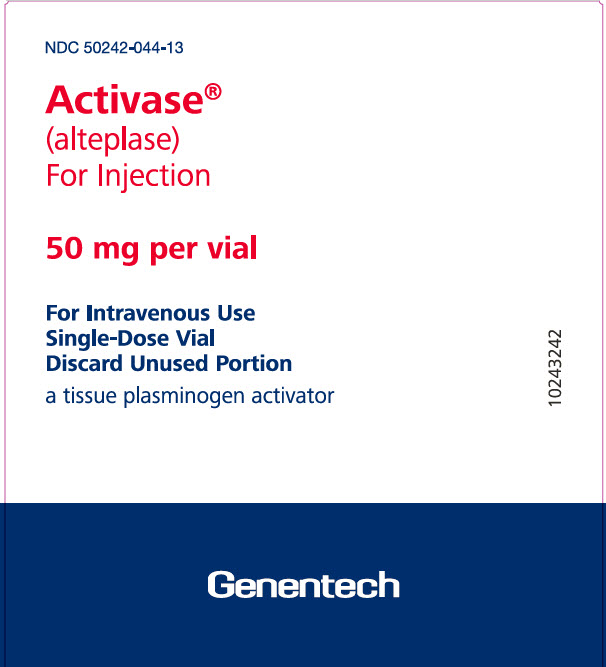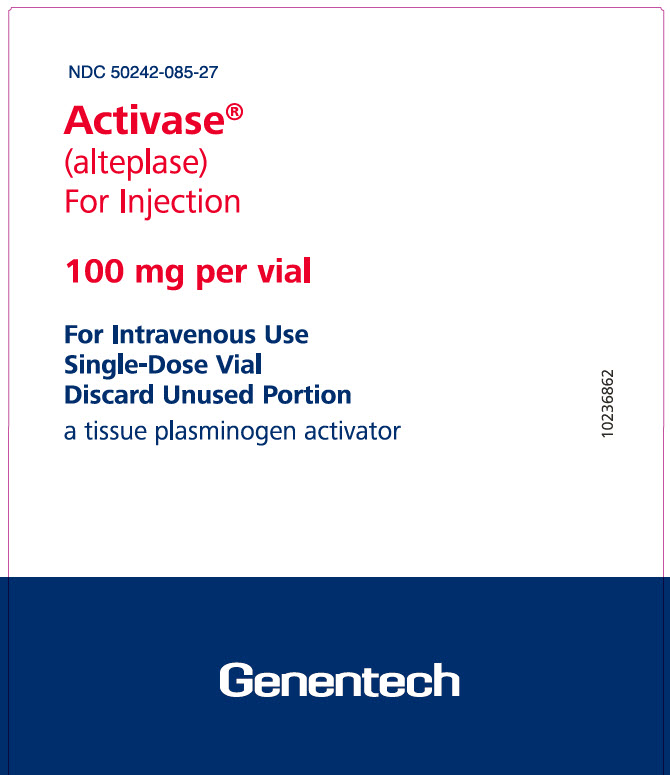 DRUG LABEL: Activase
NDC: 50242-044 | Form: KIT | Route: INTRAVENOUS
Manufacturer: Genentech, Inc.
Category: prescription | Type: HUMAN PRESCRIPTION DRUG LABEL
Date: 20260120

ACTIVE INGREDIENTS: ALTEPLASE 50 mg/50 mL
INACTIVE INGREDIENTS: ARGININE 1.7 g/50 mL; PHOSPHORIC ACID 0.5 g/50 mL; POLYSORBATE 80 4 mg/50 mL; WATER 50 mL/50 mL

HIGHLIGHTS OF PRESCRIBING INFORMATION

These highlights do not include all the information needed to use ACTIVASE safely and effectively. See full prescribing information for ACTIVASE.
Activase (alteplase) for injection, for intravenous use
Initial U.S. Approval: 1987

RECENT MAJOR CHANGES

Dosage and Administration (2.5) | 09/2022

1 INDICATIONS AND USAGE

Activase is a tissue plasminogen activator (tPA) indicated for the treatment of:

- Acute Ischemic Stroke (AIS). (1.1)
- Acute Myocardial Infarction (AMI) to reduce mortality and incidence of heart failure. (1.2)
  Limitation of Use in AMI: the risk of stroke may be greater than the benefit in patients at low risk of death from cardiac causes. (1.2)
- Acute Massive Pulmonary Embolism (PE) for lysis. (1.3)

2 DOSAGE AND ADMINISTRATION

- Acute Ischemic Stroke: The recommended dose is 0.9 mg/kg (not to exceed 90 mg total dose) infused intravenously over 60 minutes with 10% of the total dose administered as an initial bolus over 1 minute. (2.1)
- Acute Myocardial Infarction: The recommended total dose is based on patient weight, not to exceed 100 mg. (2.2)
- Acute Massive Pulmonary Embolism: The recommended dose is 100 mg administered by IV infusion over 2 hours. (2.3)

Do not add other medications to infusions containing Activase. (2.5)

3 DOSAGE FORMS AND STRENGTHS

50 mg and 100 mg lyophilized powder in single-dose vials with Sterile Water for Injection USP for reconstitution. (3)

4 CONTRAINDICATIONS

General

- Active internal bleeding. (4.1, 4.2)
- Recent intracranial or intraspinal surgery or serious head trauma. (4.1, 4.2)
- Intracranial conditions that may increase the risk of bleeding. (4.1, 4.2)
- Bleeding diathesis. (4.1, 4.2)
- Current severe uncontrolled hypertension. (4.1, 4.2)

Acute Ischemic Stroke

- Current intracranial hemorrhage. (4.1)
- Subarachnoid hemorrhage. (4.1)

Acute Myocardial Infarction or Pulmonary Embolism

- History of recent stroke. (4.2)

5 WARNINGS AND PRECAUTIONS

- Increases the risk of bleeding. Avoid intramuscular injections. Monitor for bleeding. If serious bleeding occurs, discontinue Activase. (5.1)
- Monitor patients during and for several hours after infusion for hypersensitivity. If signs of hypersensitivity develop, discontinue Activase. (5.2)
- Consider the risk of reembolization from the lysis of underlying deep venous thrombi in patients with pulmonary embolism. (5.3)
- Cholesterol embolism has been reported rarely in patients treated with thrombolytic agents. (5.4)

6 ADVERSE REACTIONS

The most frequently occurring adverse reaction (> 5%) is bleeding. (6)

To report SUSPECTED ADVERSE REACTIONS, contact Genentech at 1-888-835-2555 or FDA at 1-800-FDA-1088 or www.fda.gov/medwatch.

7 DRUG INTERACTIONS

Anticoagulants and drugs that inhibit platelet function increase the risk of bleeding when administered with Activase therapy. (7)

Concomitant angiotensin-converting enzyme inhibitors may increase the risk of angioedema. (7)

FULL PRESCRIBING INFORMATION

1 INDICATIONS AND USAGE

1.1 Acute Ischemic Stroke

Activase is indicated for the treatment of acute ischemic stroke.

Exclude intracranial hemorrhage as the primary cause of stroke signs and symptoms prior to initiation of treatment [see Contraindications (4.1)]. Initiate treatment as soon as possible but within 3 hours after symptom onset.

1.2 Acute Myocardial Infarction

Activase is indicated for use in acute myocardial infarction (AMI) for the reduction of mortality and reduction of the incidence of heart failure.

Limitation of Use: The risk of stroke may outweigh the benefit produced by thrombolytic therapy in patients whose AMI puts them at low risk for death or heart failure.

1.3 Pulmonary Embolism

Activase is indicated for the lysis of acute massive pulmonary embolism, defined as:

- Acute pulmonary emboli obstructing blood flow to a lobe or multiple lung segments.
- Acute pulmonary emboli accompanied by unstable hemodynamics, e.g., failure to maintain blood pressure without supportive measures.

2 DOSAGE AND ADMINISTRATION

2.1 Acute Ischemic Stroke

Administer Activase as soon as possible but within 3 hours after onset of symptoms.

The recommended dose is 0.9 mg/kg (not to exceed 90 mg total dose), with 10% of the total dose administered as an initial intravenous bolus over 1 minute and the remainder infused over 60 minutes.

During and following Activase administration for the treatment of acute ischemic stroke, frequently monitor and control blood pressure.

In patients without recent use of oral anticoagulants or heparin, Activase treatment can be initiated prior to the availability of coagulation study results. Discontinue Activase if the pretreatment International Normalized Ratio (INR) is greater than 1.7 or the activated partial thromboplastin time (aPTT) is elevated [see Contraindications (4.1)].

2.2 Acute Myocardial Infarction

Administer Activase as soon as possible after the onset of symptoms.

The recommended total doses for acute myocardial infarction (AMI) is based on patient weight, not to exceed 100 mg, regardless of the selected administration regimen (accelerated or 3 hour, described below).

There are two Activase dose regimens (accelerated and 3-hour) for use in the management of AMI; there are no controlled studies to compare clinical outcomes with these regimens [see Clinical Studies (14.2)].

Accelerated Infusion

The recommended accelerated infusion dose consists of an IV bolus [see Dosage and Administration (2.4, 2.5)] followed by an IV infusion as set forth in Table 1.

Table 1 Accelerated Infusion Weight-Based Doses for Patients with AMI
Patient weight | Intravenous Bolus | First 30 min | Next 60 min
> 67 kg | 15 mg | 50 mg | 35 mg
≤ 67 kg | 15 mg | 0.75 mg/kg | 0.50 mg/kg

The safety and efficacy of accelerated infusion of Activase have only been investigated with concomitant administration of heparin and aspirin [see Clinical Studies (14.2)].

3-Hour Infusion

For patients weighing ≥ 65 kg, the recommended dose is 100 mg administered as 60 mg in the first hour (6-10 mg administered as a bolus), 20 mg over the second hour, and 20 mg over the third hour. For smaller patients (< 65 kg), a dose of 1.25 mg/kg administered over 3 hours may be used. Weight-based doses are shown in Table 2.

Table 2 3-hour Infusion Weight-Based Doses for Patients with AMI
Patient weight | Bolus | Rest of 1st hour | 2nd hour | 3rd hour
≥ 65 kg | 6-10 mg | 50-54 mg | 20 mg | 20 mg
< 65 kg | 0.075 mg/kg | 0.675 mg/kg | 0.25 mg/kg | 0.25 mg/kg

2.3 Pulmonary Embolism (PE)

The recommended dose is 100 mg administered by IV infusion over 2 hours.

Institute parenteral anticoagulation near the end of or immediately following the Activase infusion when the partial thromboplastin time or thrombin time returns to twice normal or less.

2.4 Activase 50 mg Reconstitution and Administration Instructions

- Activase is for intravenous administration only.
- Do not add any other medication to infusion solutions containing Activase.
- Extravasation of Activase infusion can cause ecchymosis or inflammation. If extravasation occurs, terminate the infusion at that intravenous site and apply local therapy.
- Use within 8 hours following reconstitution (when stored at 2–30°C). Activase contains no antibacterial preservatives.

Activase 50 mg Reconstitution Notes

- Use only the accompanying Sterile Water for Injection (SWFI), USP without preservatives. Do not use Bacteriostatic Water for Injection, USP.
- Reconstitute using aseptic technique.
- Slight foaming is not unusual; let stand undisturbed for several minutes to allow large bubbles to dissipate. Inspect parenteral drug products for particulate matter and discoloration prior to administration whenever solution and container permit.
- Activase may be administered as reconstituted at 1 mg/mL or further diluted immediately before administration in an equal volume of 0.9% Sodium Chloride Injection, USP, or 5% Dextrose Injection, USP, to yield a concentration of 0.5 mg/mL, using either polyvinyl chloride bags or glass vials.
- Avoid excessive agitation during dilution; mix by gently swirling and/or slow inversion.

Activase 50 mg Reconstitution Instructions

- DO NOT USE IF VACUUM IS NOT PRESENT.
- Using a large bore needle (e.g., 18 gauge) and a syringe, reconstitute by adding the contents of the accompanying 50 mL vial of SWFI to the 50 mg vial of Activase, directing the SWFI stream into the lyophilized cake.

Activase 50 mg Preparation of Bolus Dose

- Prepare the bolus dose in one of the following ways:
  - Remove the appropriate volume from the vial of reconstituted (1 mg/mL) Activase using a syringe and needle. The syringe should not be primed with air and the needle should be inserted into the Activase vial stopper.
  - Remove the appropriate volume from a port (second injection site) on the infusion line after the infusion set is primed.
  - Program an infusion pump to deliver the appropriate volume as a bolus at the initiation of the infusion.

Activase 50 mg Administration

- Following bolus dose, if indicated [see Dosage and Administration (2.1, 2.2)]:
  - Administer using either a polyvinyl chloride bag or glass vial and infusion set.

2.5 Activase 100 mg Instructions for Use

See the enclosed Instructions for Use for Activase 100 mg enclosed in the carton for reconstitution and administration instructions.

Alternative Dilution Instructions

Activase may be administered as reconstituted at 1 mg/mL or further diluted immediately before administration in an equal volume of 0.9% Sodium Chloride Injection, USP, or 5% Dextrose Injection, USP, to yield a concentration of 0.5 mg/mL, using either polyvinyl chloride bags or glass vials.

3 DOSAGE FORMS AND STRENGTHS

- 50 mg lyophilized powder in single-dose vial with 50 mL SWFI USP for reconstitution
- 100 mg lyophilized powder in single-dose vial with 100 mL SWFI USP for reconstitution

4 CONTRAINDICATIONS

4.1 Acute Ischemic Stroke

Do not administer Activase to treat acute ischemic stroke in the following situations in which the risk of bleeding is greater than the potential benefit [see Warnings and Precautions (5.1)]:

- Current intracranial hemorrhage
- Subarachnoid hemorrhage
- Active internal bleeding
- Recent (within 3 months) intracranial or intraspinal surgery or serious head trauma
- Presence of intracranial conditions that may increase the risk of bleeding (e.g., some neoplasms, arteriovenous malformations, or aneurysms)
- Bleeding diathesis
- Current severe uncontrolled hypertension.

4.2 Acute Myocardial Infarction or Pulmonary Embolism

Do not administer Activase for treatment of AMI or PE in the following situations in which the risk of bleeding is greater than the potential benefit [see Warnings and Precautions (5.1)]:

- Active internal bleeding
- History of recent stroke
- Recent (within 3 months) intracranial or intraspinal surgery or serious head trauma
- Presence of intracranial conditions that may increase the risk of bleeding (e.g. some neoplasms, arteriovenous malformations, or aneurysms)
- Bleeding diathesis
- Current severe uncontrolled hypertension.

5 WARNINGS AND PRECAUTIONS

5.1 Bleeding

Activase can cause significant, sometimes fatal, internal or external bleeding, especially at arterial and venous puncture sites. Avoid intramuscular injections and trauma to the patient while on Activase. Perform venipunctures carefully and only as required. To minimize bleeding from noncompressible sites, avoid internal jugular and subclavian venous punctures. If an arterial puncture is necessary during Activase infusion, use an upper extremity vessel that is accessible to manual compression, apply pressure for at least 30 minutes, and monitor the puncture site closely.

Because of the higher risk of intracranial hemorrhage in patients treated for acute ischemic stroke, limit treatment to facilities that can provide timely access to appropriate evaluation and management of intracranial hemorrhage.

Fatal cases of hemorrhage associated with traumatic intubation in patients administered Activase have been reported.

Aspirin and heparin have been administered concomitantly with and following infusions of Activase in the management of acute myocardial infarction and pulmonary embolism, but the concomitant administration of heparin and aspirin with and following infusions of Activase for the treatment of acute ischemic stroke during the first 24 hours after symptom onset has not been investigated. Because heparin, aspirin, or Activase may cause bleeding complications, carefully monitor for bleeding, especially at arterial puncture sites. Hemorrhage can occur 1 or more days after administration of Activase, while patients are still receiving anticoagulant therapy.

If serious bleeding occurs, terminate the Activase infusion and treat appropriately. In the following conditions, the risks of bleeding with Activase therapy for all approved indications are increased and should be weighed against the anticipated benefits:

- Recent major surgery or procedure, (e.g., coronary artery bypass graft, obstetrical delivery, organ biopsy, previous puncture of noncompressible vessels)
- Cerebrovascular disease
- Recent intracranial hemorrhage
- Recent gastrointestinal or genitourinary bleeding
- Recent trauma
- Hypertension: systolic BP above 175 mm Hg or diastolic BP above 110 mm Hg
- Acute pericarditis
- Subacute bacterial endocarditis
- Hemostatic defects including those secondary to severe hepatic or renal disease
- Significant hepatic dysfunction
- Pregnancy
- Diabetic hemorrhagic retinopathy, or other hemorrhagic ophthalmic conditions
- Septic thrombophlebitis or occluded AV cannula at seriously infected site
- Advanced age [see Use in Specific Populations (8.5)]
- Patients currently receiving anticoagulants (e.g., warfarin sodium)

Any other condition in which bleeding constitutes a significant hazard or would be particularly difficult to manage because of its location.

5.2 Hypersensitivity

Hypersensitivity, including urticarial / anaphylactic reactions, have been reported after administration of Activase (e.g., laryngeal edema, rash and shock). Rare fatal outcome for hypersensitivity was reported. Angioedema has been observed during and up to 2 hours after Activase infusion in patients treated for acute ischemic stroke and acute myocardial infarction. In many cases, patients received concomitant angiotensin-converting enzyme inhibitors [see Drug Interactions (7)].

Monitor patients treated with Activase during and for several hours after infusion for hypersensitivity. If signs of hypersensitivity occur, e.g. anaphylactoid reaction or angioedema develops, discontinue the Activase infusion and promptly institute appropriate therapy (e.g., antihistamines, intravenous corticosteroids, epinephrine).

5.3 Thromboembolism

The use of thrombolytics can increase the risk of thrombo-embolic events in patients with high likelihood of left heart thrombus, such as patients with mitral stenosis or atrial fibrillation. Activase has not been shown to treat adequately underlying deep vein thrombosis in patients with PE. Consider the possible risk of re-embolization due to the lysis of underlying deep venous thrombi in this setting.

5.4 Cholesterol Embolization

Cholesterol embolism has been reported rarely in patients treated with thrombolytic agents; the true incidence is unknown. Cholesterol embolism may present with livedo reticularis, "purple toe" syndrome, acute renal failure, gangrenous digits, hypertension, pancreatitis, myocardial infarction, cerebral infarction, spinal cord infarction, retinal artery occlusion, bowel infarction, or rhabdomyolysis and can be fatal. It is associated with invasive vascular procedures (e.g., cardiac catheterization, angiography, vascular surgery) and/or anticoagulant therapy.

5.5 Coagulation Tests May Be Unreliable during Activase Therapy

Coagulation tests and measures of fibrinolytic activity may be unreliable during Activase therapy, unless specific precautions are taken to prevent in vitro artifacts. When present in blood at pharmacologic concentrations, Activase remains active under in vitro conditions, which can result in degradation of fibrinogen in blood samples removed for analysis.

6 ADVERSE REACTIONS

The following adverse reactions are discussed in greater detail in the other sections of the label:

- Bleeding [see Contraindications (4), Warnings and Precautions (5.1)]
- Hypersensitivity [see Warnings and Precautions (5.2)]
- Thromboembolism [see Warnings and Precautions (5.3)]
- Cholesterol Embolization [see Warnings and Precautions (5.4)]

6.1 Clinical Trials Experience

Because clinical trials are conducted under widely varying conditions, adverse reaction rates observed in the clinical trials of a drug cannot be directly compared to rates in the clinical trials of another drug and may not reflect the rates observed in clinical practice.

The most frequent adverse reaction associated with Activase in all approved indications is bleeding.

Bleeding

Acute Ischemic Stroke (AIS)

In clinical studies in patients with AIS (Studies 1 and 2) the incidence of intracranial hemorrhage, especially symptomatic intracranial hemorrhage, was higher in Activase-treated patients than in placebo patients. A dose-finding study of Activase suggested that doses greater than 0.9 mg/kg may be associated with an increased incidence of intracranial hemorrhage.

The incidence of all-cause 90-day mortality, intracranial hemorrhage, and new ischemic stroke following Activase treatment compared to placebo are presented in Table 3 as a combined safety analysis (n=624) for Studies 1 and 2. These data indicate a significant increase in intracranial hemorrhage following Activase treatment, particularly symptomatic intracranial hemorrhage within 36 hours. There was no increase in the incidences of 90-day mortality or severe disability in Activase-treated patients compared to placebo.

Table 3 Combined Safety Outcomes for Studies 1 and 2
 | Placebo (n= 312) | Activase (n=312) | p-Value [Fisher's Exact Test.]
All-Cause 90-day Mortality | 64 (20.5%) | 54 (17.3%) | 0.36
Total ICH [Within trial follow-up period. Symptomatic intracranial hemorrhage was defined as the occurrence of sudden clinical worsening followed by subsequent verification of intracranial hemorrhage on CT scan. Asymptomatic intracranial hemorrhage was defined as intracranial hemorrhage detected on a routine repeat CT scan without preceding clinical worsening.] | 20 (6.4%) | 48 (15.4%) | <0.01
Symptomatic | 4 (1.3%) | 25 (8.0%) | <0.01
Asymptomatic | 16 (5.1%) | 23 (7.4%) | 0.32
Symptomatic Intracranial Hemorrhage within 36 hours | 2 (0.6%) | 20 (6.4%) | <0.01
New Ischemic Stroke (3-months) | 17 (5.4%) | 18 (5.8%) | 1.00

Bleeding events other than intracranial hemorrhage were noted in the studies of AIS and were consistent with the general safety profile of Activase. In Studies 1 and 2, the frequency of bleeding requiring red blood cell transfusions was 6.4% for Activase-treated patients compared to 3.8% for placebo (p = 0.19).

Although exploratory analyses of Studies 1 and 2 suggest that severe neurological deficit (National Institutes of Health Stroke Scale [NIHSS > 22]) at presentation was associated with an increased risk of intracranial hemorrhage, efficacy results suggest a reduced but still favorable clinical outcome for these patients.

Acute Myocardial Infarction (AMI)

For the 3-hour infusion regimen in the treatment of AMI, the incidence of significant internal bleeding (estimated as > 250 mL blood loss) has been reported in studies in over 800 patients (Table 4). These data do not include patients treated with the Activase accelerated infusion.

Table 4 Incidence of Bleeding in 3-Hour Infusion in AMI Patients
 | Total Dose ≤100 mg
Gastrointestinal | 5%
Genitourinary | 4%
Ecchymosis | 1%
Retroperitoneal | <1%
Epistaxis | <1%
Gingival | <1%

The incidence of intracranial hemorrhage in AMI patients treated with Activase is presented in Table 5.

Table 5 Incidence of Intracranial Hemorrhage in AMI Patients
Dose | Number of Patients | Intracranial Hemorrhage (%)
100 mg, 3-hour | 3272 | 0.4
≤ 100 mg, accelerated | 10,396 | 0.7
150 mg | 1779 | 1.3
1-1.4 mg/kg | 237 | 0.4

A dose of 150 mg or greater should not be used in the treatment of AMI because it has been associated with an increase in intracranial bleeding.

Pulmonary Embolism (PE)

For acute massive pulmonary embolism, bleeding events were consistent with the general safety profile observed with Activase treatment of AMI patients receiving the 3-hour infusion regimen.

6.2 Post-Marketing Experience

The following adverse reactions have been identified during post-approval use of Activase. Because these reactions are reported voluntarily from a population of uncertain size, it is not always possible to reliably estimate their frequency or establish a causal relationship to drug exposure. These reactions are frequent sequelae of the underlying disease, and the effect of Activase on the incidence of these events is unknown.

Acute Ischemic Stroke: Cerebral edema, cerebral herniation, seizure, new ischemic stroke, embolism. These events may be life threatening and may lead to death.

Acute Myocardial Infarction: Arrhythmias, AV block, cardiogenic shock, heart failure, cardiac arrest, recurrent ischemia, myocardial reinfarction, myocardial rupture, electromechanical dissociation, pericardial effusion, pericarditis, mitral regurgitation, cardiac tamponade, thromboembolism, pulmonary edema. These events may be life threatening and may lead to death. Nausea and/or vomiting, hypotension and fever have also been reported.

Pulmonary Embolism: Pulmonary reembolization, pulmonary edema, pleural effusion, thromboembolism, hypotension. These events may be life threatening and may lead to death. Fever has also been reported.

7 DRUG INTERACTIONS

The interaction of Activase with other cardioactive or cerebroactive drugs has not been studied. Anticoagulants and antiplatelet drugs increase the risk of bleeding if administered prior to, during, or after Activase therapy.

In the post-marketing setting, there have been reports of angioedema in patients (primarily patients with AIS) receiving concomitant angiotensin-converting enzyme inhibitors. [see Warnings and Precautions (5.2)].

8 USE IN SPECIFIC POPULATIONS

8.1 Pregnancy

Risk Summary

Published studies and case reports on alteplase use in pregnant women are insufficient to inform a drug associated risk of adverse developmental outcomes. Alteplase is embryocidal in rabbits when intravenously administered during organogenesis at the clinical exposure for AMI, but no maternal or fetal toxicity was evident at lower exposure in pregnant rats or rabbits (see Data).

All pregnancies have a background risk of birth defect, loss, or other adverse outcomes. The estimated background risk of major birth defects and miscarriage for the indicated populations is unknown. In the U.S. general population, the estimated background risk of major birth defects and miscarriage in clinically recognized pregnancies is 2-4% and 15-20%, respectively.

Clinical Considerations

Maternal Adverse Reactions

The most common complication of thrombolytic therapy is bleeding. Pregnancy may increase this risk [see Warnings and Precautions (5.1)].

Data

Animal Data

Alteplase is embryocidal in rabbits when administered intravenously during organogenesis in doses (3 mg/kg) approximately equal to the human exposure (based on AUC) at the dose for AMI. No maternal or fetal toxicity was evident at doses (1 mg/kg) approximately 0.3 times the human exposure. In pregnant rats, no maternal or fetal toxicity was evident at doses (1 mg/kg) approximately 0.6 times the human dose for AMI (based on body weight) dosed during the period of organogenesis.

8.2 Lactation

Risk Summary

There are no data on the presence of alteplase in human milk, the effects on the breastfed infant, or the effects on milk production.

8.4 Pediatric Use

Safety and effectiveness of Activase in pediatric patients have not been established.

8.5 Geriatric Use

Acute Ischemic Stroke

In exploratory, multivariate analyses of Studies 1 and 2, age greater than 77 years was one of several interrelated baseline characteristics associated with an increased risk of intracranial hemorrhage. Efficacy results suggest a reduced but still favorable clinical outcome for Activase-treated elderly [see Clinical Studies (14.1)].

Acute Myocardial Infarction

In a large trial of accelerated-infusion Activase that enrolled 41,021 patients with AMI to one of four thrombolytic regimens [see Clinical Studies (14.2)], patients over 75 years of age, a predefined subgroup, comprised 12% of enrollment. In these patients, the incidence of stroke was 4.0% for the Activase accelerated infusion group, 2.8% for streptokinase IV [SK (IV)], and 3.2% for streptokinase SQ [SK (SQ)]. The incidence of combined 30-day mortality or nonfatal stroke was 20.6% for accelerated infusion of Activase, 21.5% for SK (IV), and 22.0% for SK (SQ).

11 DESCRIPTION

Alteplase is a tissue plasminogen activator produced by recombinant DNA technology. It is a sterile, purified glycoprotein of 527 amino acids. It is synthesized using the complementary DNA (cDNA) for natural human tissue-type plasminogen activator obtained from a human melanoma cell line. Biological potency is determined by an in vitro clot lysis assay and is expressed in International Units (IU).

Activase (alteplase) is a sterile, white to off-white, lyophilized powder for intravenous administration after reconstitution with Sterile Water for Injection, USP.

Table 6 Quantitative Composition of the Lyophilized Product
 | 100 mg Vial | 50 mg Vial
Alteplase | 100 mg (58 million IU) | 50 mg (29 million IU)
L-Arginine | 3.5 g | 1.7 g
Phosphoric Acid | 1 g | 0.5 g
Polysorbate 80 | 10 mg | 5 mg
Vacuum | No | Yes

The reconstituted preparation results in a colorless to pale yellow transparent solution containing Activase 1 mg/mL at approximately pH 7.3. The osmolality of this solution is approximately 215 mOsm/kg.

12 CLINICAL PHARMACOLOGY

12.1 Mechanism of Action

Alteplase is a serine protease responsible for fibrin-enhanced conversion of plasminogen to plasmin. It produces limited conversion of plasminogen in the absence of fibrin.

When introduced into the systemic circulation at pharmacologic concentration, alteplase binds to fibrin in a thrombus and converts the entrapped plasminogen to plasmin. This initiates local fibrinolysis with limited systemic proteolysis.

12.2 Pharmacodynamics

Following administration of 100 mg Activase, there is a decrease (16%-36%) in circulating fibrinogen. In a controlled trial, 8 of 73 patients (11%) receiving Activase (1.25 mg/kg body weight over 3 hours) experienced a decrease in fibrinogen to below 100 mg/dL.

12.3 Pharmacokinetics

Alteplase in acute myocardial infarction (AMI) patients is rapidly cleared from the plasma with an initial half-life of less than 5 minutes. There is no difference in the dominant initial plasma half-life between the 3-hour and accelerated regimens for AMI. The plasma clearance of alteplase is 380-570 mL/min, primarily mediated by the liver. The initial volume of distribution approximates plasma volume.

13 NONCLINICAL TOXICOLOGY

13.1 Carcinogenesis, Mutagenesis, Impairment of Fertility

Long-term studies in animals have not been performed to evaluate the carcinogenic potential or the effect on fertility. Short-term studies, which evaluated tumorigenicity of Activase and effect on tumor metastases in rodents, were negative.

Studies to determine mutagenicity (Ames test) and chromosomal aberration assays in human lymphocytes were negative at all concentrations tested. Cytotoxicity, as reflected by a decrease in mitotic index, was evidenced only after prolonged exposure and only at the highest concentrations tested.

14 CLINICAL STUDIES

14.1 Acute Ischemic Stroke (AIS)

Two placebo-controlled, double-blind trials (Studies 1 and 2) were conducted in patients with AIS. Both studies enrolled patients with measurable neurological deficit who could complete screening and begin study treatment within 3 hours from symptom onset. A cranial computerized tomography (CT) scan was performed prior to treatment to rule out the presence of intracranial hemorrhage. Blood pressure was actively controlled (185/110 mm Hg or lower) for 24 hours.

Patients were randomized (1:1) to receive either 0.9 mg/kg Activase (maximum of 90 mg) or placebo. Activase was administered as a 10% initial IV bolus over 1 minute followed by continuous IV infusion of the remainder over 60 minutes. Study treatment was initiated prior to the availability of coagulation study results in patients without recent use of oral anticoagulants and/or heparin and was discontinued if the pretreatment prothrombin time (PT) was greater than 15 seconds or the activated partial thromboplastin time (aPTT) was elevated. Patients with prior aspirin use were included. Administration of anticoagulants and antiplatelet agents was prohibited for the first 24 hours following symptom onset.

Study 1 (n=291) evaluated neurological improvement at 24 hours after stroke onset. The primary endpoint, the proportion of patients with a 4 point or greater improvement in the National Institutes of Health Stroke Scale (NIHSS) score or complete recovery (NIHSS score of 0), was not significantly different between treatment groups. A prespecified secondary analysis suggested improved 3-month outcome associated with Activase treatment using the following stroke assessment scales: Barthel Index, Modified Rankin Scale, Glasgow Outcome Scale, and the NIHSS.

Study 2 (n=333) assessed clinical outcome at 3 months. A favorable outcome was defined as minimal or no disability using four stroke assessment scales: Barthel Index (score of 95 or greater), Modified Rankin Scale (score of 1 or less), Glasgow Outcome Scale (score of 1), and NIHSS (score of 1 or less). The results comparing Activase- and placebo-treated patients for the four outcome scales together (Generalized Estimating Equations) and individually are presented in Table 7. In this study, depending upon the scale, the favorable outcome of minimal or no disability occurred in at least 11 per 100 more patients treated with Activase than those receiving placebo. Study results demonstrated consistent functional and neurological improvement within all four stroke scales as indicated by median scores. These results were consistent with the 3-month outcome treatment effects observed in Study 1.

Table 7 Study 2 Three-Month Efficacy Outcomes
Analysis | Frequency of Favorable Outcome [Favorable Outcome is defined as recovery with minimal or no disability.]
Analysis | Placebo (n=165) | Activase (n=168) | Absolute Difference (95% CI) | Odds Ratio [Value greater than 1 indicates odds of recovery in favor of Activase treatment.] (95% Cl) | p-Value [p-Value for Odds Ratio is from Generalized Estimating Equations with logit link.]
Generalized Estimating Equations (Multivariate) | - | - | - | 1.71 (1.15, 2.56) | 0.02
Barthel Index | 37.6% | 50.0% | 12.4% (3.0, 21.9) | 1.66 (1.07, 2.57) | 0.02
Modified Rankin Scale | 26.1% | 38.7% | 12.6% (3.7, 21.6) | 1.79 (1.12, 2.85) | 0.02
Glasgow Outcome Scale | 31.5% | 44.0% | 12.5% (3.3, 21.8) | 1.71 (1.09, 2.68) | 0.02
NIHSS | 20.0% | 31.0% | 11.0% (2.6, 19.3) | 1.79 (1.06, 2.96) | 0.02

In a prespecified subgroup analysis of patients receiving aspirin prior to onset of stroke symptoms, the favorable outcome for Activase-treated patients was preserved.

14.2 Acute Myocardial Infarction (AMI)

Two Activase dose regimens have been studied in patients experiencing acute myocardial infarction [see Dosage and Administration (2.2)]. The comparative efficacy of these two regimens has not been evaluated.

Accelerated Infusion in AMI Patients

Accelerated infusion of Activase was studied in an international, multi-center trial that randomized 41,021 patients with AMI to four thrombolytic regimens (Study 3). Entry criteria included onset of chest pain within 6 hours of treatment and ST-segment elevation of ECG. The four treatment regimens included accelerated infusion of Activase (≤100 mg over 90 minutes) plus intravenous (IV) heparin (n = 10,396); Streptokinase (1.5 million units over 60 minutes) plus IV heparin (SK [IV], n =10,410); Streptokinase plus subcutaneous (SQ) heparin (SK [SQ] n= 9841). A fourth regimen combined Activase and Streptokinase (n =10,374). All patients received 160 mg chewable aspirin administered as soon as possible, followed by 160-325 mg daily. Bolus IV heparin 5000 U was initiated as soon as possible, followed by a 1000 U/hour continuous IV infusion for at least 48 hours; subsequent heparin therapy was at the physician's discretion. Heparin SQ 12,500 U was administered 4 hours after initiation of SK therapy, followed by 12,500 U twice daily for 7 days or until discharge, whichever came first. Many of the patients randomized to receive SQ heparin received some IV heparin, usually in response to recurrent chest pain and/or the need for a medical procedure. Some received IV heparin on arrival to the emergency room prior to enrollment and randomization.

Key results from Study 3 are shown in Table 8. The incidence of 30-day mortality for Activase accelerated infusion was 1.0% lower than for either Streptokinase plus heparin regimen. The incidence of combined 30-day mortality or nonfatal stroke for the Activase accelerated infusion was 1.0% lower than for SK (IV) and 0.8% lower than for SK (SQ).

Table 8 Efficacy and Safety Results for Study 3
Event | Accelerated Activase | SK (IV) | p-Value [Two-tailed p-value is for comparison of Accelerated Activase to the respective SK control arm.] | SK (SQ) | p-Value
30-Day Mortality | 6.3% | 7.3% | 0.003 | 7.3% | 0.007
30-Day Mortality or Nonfatal Stroke | 7.2% | 8.2% | 0.006 | 8.0% | 0.036
24-Hour Mortality | 2.4% | 2.9% | 0.009 | 2.8% | 0.029
Any Stroke | 1.6% | 1.4% | 0.32 | 1.2% | 0.03
Intracerebral Hemorrhage | 0.7% | 0.6% | 0.22 | 0.5% | 0.02

Subgroup analysis of patients by age, infarct location, time from symptom onset to thrombolytic treatment, and treatment in the U.S. or elsewhere showed consistently lower 30-day mortality on Activase.

For patients who were over 75 years of age, a predefined subgroup consisting of 12% of patients enrolled, the incidence of stroke was 4.0% for the Activase accelerated infusion group, 2.8% for SK (IV), and 3.2% for SK (SQ); the incidence of combined 30-day mortality or nonfatal stroke was 20.6% for accelerated infusion of Activase, 21.5% for SK (IV), and 22.0% for SK (SQ).

3-Hour Infusion in AMI Patients

In a double-blind, randomized trial (n = 138) comparing 3-hour infusion of Activase to placebo (Study 4), patients infused with Activase within 4 hours of onset of symptoms experienced improved left ventricular function at Day 10 compared to the placebo group, when ejection fraction was measured by gated blood pool scan (53.2% vs. 46.4%, p =0.018). Relative to baseline (Day 1) values, the net changes in ejection fraction were + 3.6% and -4.7% for the treated and placebo groups, respectively (p=0.0001). The treated group had a reduced incidence of clinical heart failure (14%) compared to the placebo group (33%) (p = 0.009).

In a double-blind, randomized trial (n =5013) comparing 3-hour infusion of Activase to placebo (Study 5), patients infused with Activase within 5 hours of AMI symptom onset experienced improved 30-day survival compared to the placebo arm. At 1 month, the overall mortality rates were 7.2% for the Activase group and 9.8% for the placebo group (p = 0.001). At 6 months, the overall mortality rate for Activase-treated patients was 10.4% compared to the placebo arm (13.1%, p= 0.008).

14.3 Acute Massive Pulmonary Embolism (PE)

Study 6 was a comparative randomized trial (n =45) in which 59% of patients (n =22) treated with Activase (100 mg over 2 hours) experienced moderate or marked lysis of pulmonary emboli when assessed by pulmonary angiography 2 hours after treatment initiation. Activase-treated patients also experienced a significant reduction in pulmonary embolism-induced pulmonary hypertension within 2 hours of treatment (p=0.003). Pulmonary perfusion at 24 hours, as assessed by radionuclide scan, was significantly improved (p= 0.002).

16 HOW SUPPLIED/STORAGE AND HANDLING

16.1 How Supplied

Activase is supplied as a sterile, lyophilized powder in 50 mg single-dose vials containing vacuum and in 100 mg single-dose vials without vacuum.

Each 50 mg Activase vial (29 million IU) is packaged with diluent for reconstitution (50 mL Sterile Water for Injection, USP): NDC 50242-044-13.

Each 100 mg Activase vial (58 million IU) is packaged with diluent for reconstitution (100 mL Sterile Water for Injection, USP), and one transfer device: NDC 50242-085-27.

16.2 Stability and Storage

Store lyophilized Activase at controlled room temperature not to exceed 30°C (86°F), or under refrigeration at 2° to 8°C (36° to 46°F). Protect the lyophilized material during extended storage from excessive exposure to light. If stored between 2-30°C (36-86°F), Activase may be used within 8 hours following reconstitution. Discard any unused solution after administration is complete.

Do not use beyond the expiration date stamped on the vial.

17 PATIENT COUNSELING INFORMATION

Following Activase administration, patients are at increased risk of bleeding internally or externally. Advise patients to contact a health-care professional if they experience symptoms or signs consistent with bleeding (e.g., unusual bruising, pink or brown urine, red or black or tarry stools, coughing up blood, vomiting blood or blood that looks like coffee grounds), headache, or stroke symptoms.

Activase® (alteplase)
Manufactured by:
Genentech, Inc.
A Member of the Roche Group
1 DNA Way
South San Francisco, CA
94080-4990
U.S. License No. 1048

Activase® is a registered trademark of Genentech, Inc.
©2022 Genentech, Inc.

INSTRUCTIONS FOR USE

Activase®
(alteplase) for injection
for intravenous use

100 mg (58 million IU)

Read before preparing Activase®

See also enclosed, full prescribing information

Instructions for Use should accompany reconstituted Activase to patient bedside.

Kit Contents

Transfer device

Activase vial
(no vacuum)

Activase vial stopper parts:

Sterile Water for Injection (water) vial
Note: Do not use Bacteriostatic Water for Injection, USP.

Prescribing Information
Instructions for Use

Also Required

(not included in kit)

1 Luer syringe for removing bolus dose, as needed

1 Luer syringe for removing excess volume, as needed

2 large bore needles

2 Alcohol swabs

IV infusion set

Reconstitution (use aseptic technique)
Step 1: Cleaning | Step 2: Spiking Water vial | Step 3: Spiking Activase vial
- Remove caps from both vials. - Wipe each stopper with a separate alcohol swab. | - Remove cover from one end of transfer device. Do not wipe transfer device spikes with alcohol. (Note: Either side of transfer device can be used). - Insert spike straight through center of water vial stopper.; Do not invert water vial yet. Inverting too early may lead to leakage and incorrect dosing. | - Remove cover from other end of transfer device. - Hold Activase vial upside down over spike. - Press Activase vial down to insert spike straight through center of Activase vial stopper.; Inserting the spike off-center could lead to stopper collapse.
Reconstitution (use aseptic technique) |  | Administration Warning
Step 4: Inverting and transferring | Step 5: Inspecting
- Invert vials so that water vial is on top. - Allow all water to transfer into Activase vial. - If the flow does not start immediately or pauses, initiate the flow by flipping and re-inverting the vials. - Swirl gently and/or invert slowly to dissolve Activase powder.; Do not shake vials. Shaking may lead to excessive foaming and degraded medication. | - Separate empty water vial and transfer device from Activase vial. - Reconstituted Activase vial (1 mg/mL) should be: - Colorless to pale yellow and transparent - Free of particulates - If needed, let stand undisturbed for a few minutes to allow large bubbles to dissipate. | Review important information below before continuing to Step 6. Do not push air from the syringe into the vial. The vial is not under vacuum and adding air at any time may result in leakage and incorrect dosing. Only insert needles within center ring of stopper, away from hole made by transfer device. Insert needle within center ring of stopper, away from the hole made by transfer device when withdrawing medication to avoid leakage and incorrect dosing. Do not insert needles outside of the center ring of stopper.
Administration (use aseptic technique)
Step 6: Preparing bolus | Step 7: Removing excess volume | Step 8: Spiking and hanging
- Check if bolus is needed. If yes, attach needle to empty Luer syringe. - Insert needle once through center ring of stopper, away from hole made by transfer device, and slowly withdraw the bolus amount. | - Check if there is excess volume in vial. If yes, attach needle to empty Luer syringe. - Insert needle once through center ring of stopper, away from hole made by transfer device, and slowly withdraw the excess volume. | - Insert spike from IV tubing set into center of vial stopper, through same hole made by transfer device.
Do not push any air from syringe into vial (may cause leakage). | Do not push any air from syringe into vial (may cause leakage). | Do not make a new hole in the vial stopper. Additional holes in vial stopper may lead to leakage.
- Alternatively, the bolus can be left in the vial and administered via an infusion pump or removed from a port on the infusion line. | - Discard any excess volume. - Leave infusion dose in vial. | - Peel clear plastic hanger from vial label. - Hang on IV pole and administer per facility protocol.

Administration Notes

- Activase is for intravenous administration only.
- Do not add any other medication to infusion solutions containing Activase.
- Extravasation of Activase infusion can cause ecchymosis or inflammation. If extravasation occurs, terminate the infusion at that IV site and apply local therapy.
- See full prescribing information for alternative dilution instructions.

Storage & Stability

- Store lyophilized Activase at controlled room temperature not to exceed 30°C (86°F), or under refrigeration at 2° to 8° C (36° to 46° F). Protect the lyophilized material during extended storage from excessive exposure to light.
- Activase contains no antibacterial preservatives and must be used within 8 hours following reconstitution (when stored at 2-30°C).

Manufactured by:
Genentech, Inc.
A Member of the Roche Group
1 DNA Way
South San Francisco, CA 94080-4990

U.S. License No. 1048

Activase® (alteplase) is a registered trademark of Genentech, Inc.

©2025 Genentech, Inc. All rights reserved.

This Instructions for Use has been approved by the U.S. Food and Drug Administration.

Revised: February/2025

Representative sample of labeling (see the HOW SUPPLIED section for complete listing):

PRINCIPAL DISPLAY PANEL - Kit Carton - 50 mg

NDC 50242-044-13

Activase®
(alteplase)
For Injection

50 mg per vial

For Intravenous Use
Single-Dose Vial
Discard Unused Portion

a tissue plasminogen activator

10243242

Genentech

PRINCIPAL DISPLAY PANEL - Kit Carton - 100 mg

NDC 50242-085-27

Activase®
(alteplase)
For Injection

100 mg per vial

For Intravenous Use
Single-Dose Vial
Discard Unused Portion

a tissue plasminogen activator

10236862

Genentech